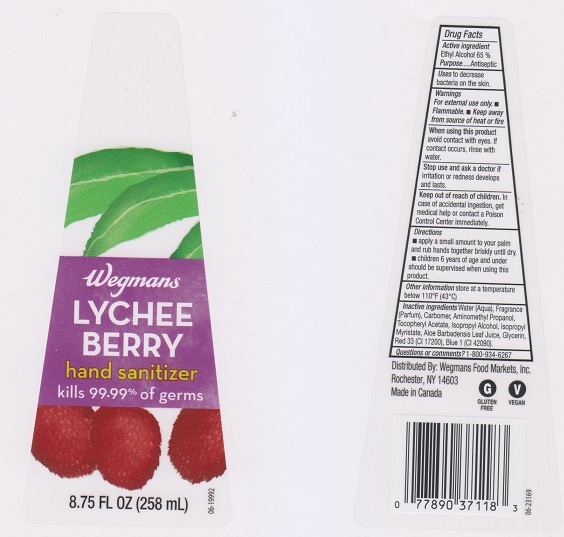 DRUG LABEL: Wegmans
NDC: 47124-407 | Form: LIQUID
Manufacturer: Wegmans Food Markets Inc
Category: otc | Type: HUMAN OTC DRUG LABEL
Date: 20170523

ACTIVE INGREDIENTS: ALCOHOL 650 mg/1 mL
INACTIVE INGREDIENTS: WATER; CARBOMER 934; AMINOMETHYLPROPANOL; .ALPHA.-TOCOPHEROL ACETATE, DL-; ISOPROPYL ALCOHOL; ISOPROPYL MYRISTATE; ALOE VERA LEAF; GLYCERIN; D&C RED NO. 33; FD&C BLUE NO. 1

Drug Facts

Active ingredient

Ethyl Alcohol 65%

Purpose

Antiseptic

Uses

to decrease bacteria on the skin.

Warnings

For external use only

- Flammable
- Keep away from source of heat or fire

When using this product

avoid contact with eyes. If contact occurs, rinse with water.

Stop use and ask a doctor if

irritation or redness develops and lasts.

Keep out of reach of children.

In case of accidental ingestion, get medical help or contact a Poison Control Center immediately.

Directions

- apply a small amount to your palm and rub hands together briskly until dry.
- children 6 years of age and under should be supervised when using this product.

Other information

store at a temperature below 110°F (43°C)

Inactive ingredients

Water (Aqua), Fragrance (Parfum), Carbomer, Aminomethyl Propanol, Tocopheryl Acetate, Isopropyl Alcohol, Isopropyl Myristate, Aloe Barbadensis Leaf Juice, Glycerin, Red 33 (CI 17200), Blue 1 (CI 42090).

Questions or comments?

1-800-934-6267